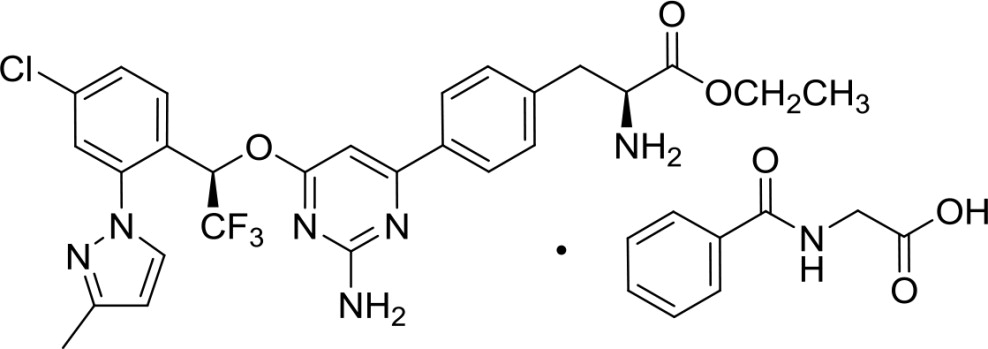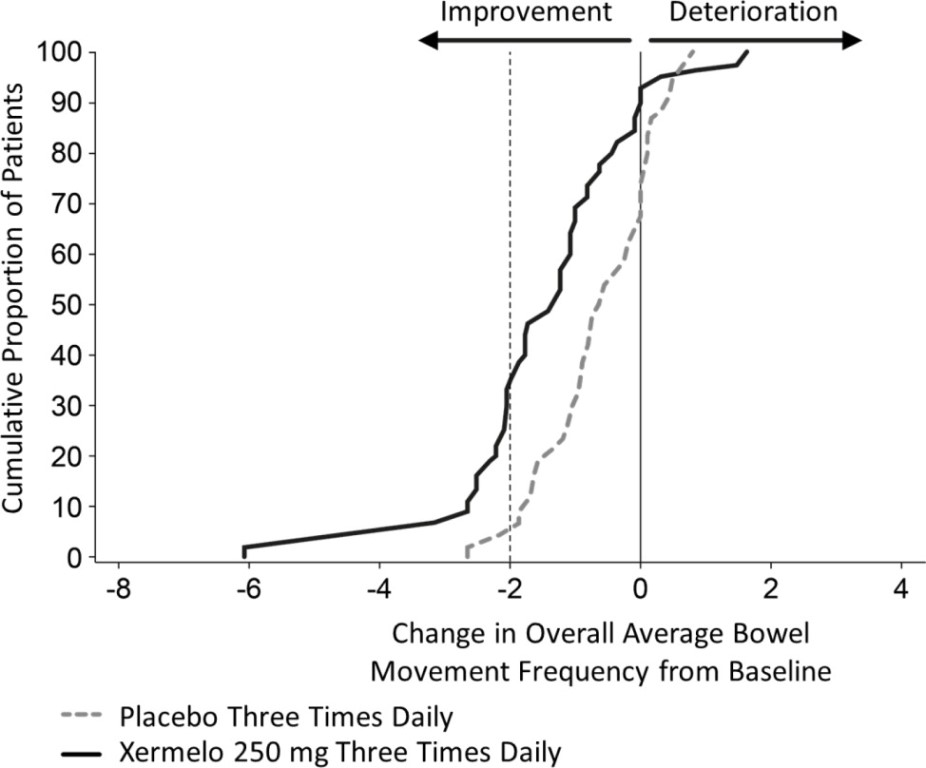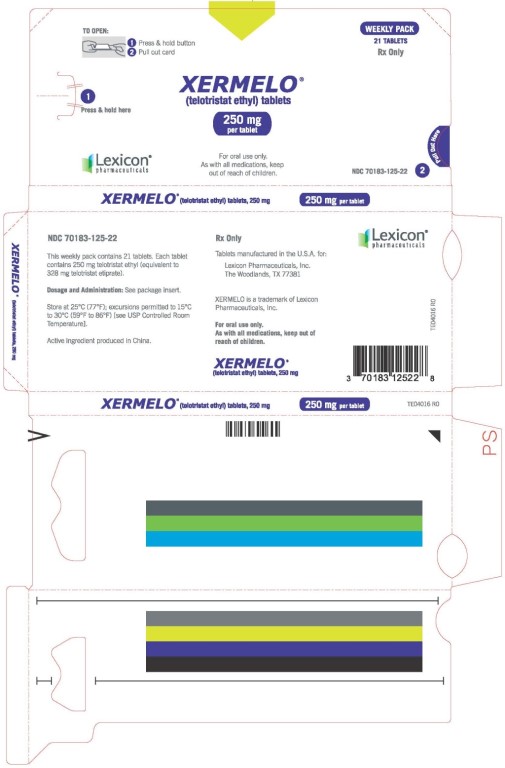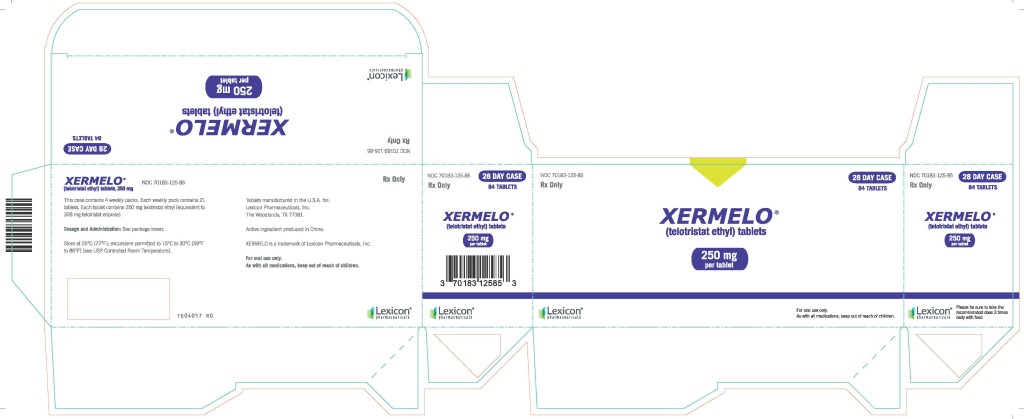 DRUG LABEL: Xermelo
NDC: 70183-125 | Form: TABLET
Manufacturer: Lexicon Pharmaceuticals, Inc.
Category: prescription | Type: HUMAN PRESCRIPTION DRUG LABEL
Date: 20251001

ACTIVE INGREDIENTS: telotristat ethyl 250 mg/1 1
INACTIVE INGREDIENTS: anhydrous lactose; hydroxypropyl cellulose (90000 wamw); croscarmellose sodium; magnesium stearate; silicon dioxide; polyvinyl alcohol, unspecified; titanium dioxide; polyethylene glycol, unspecified; talc

HIGHLIGHTS OF PRESCRIBING INFORMATION

These highlights do not include all the information needed to use XERMELO safely and effectively. See full prescribing information for XERMELO.
XERMELO (telotristat ethyl) tablets, for oral use
Initial U.S. Approval: 2017

1 INDICATIONS AND USAGE

Xermelo is a tryptophan hydroxylase inhibitor indicated for the treatment of carcinoid syndrome diarrhea in combination with somatostatin analog (SSA) therapy in adults inadequately controlled by SSA therapy. (1)

2 DOSAGE AND ADMINISTRATION

- The recommended dosage of Xermelo in adult patients is 250 mg three times daily for patients whose diarrhea is inadequately controlled by a SSA therapy. (2)
- Take Xermelo with food. (2)
- When short-acting octreotide is used in combination with Xermelo, administer short-acting octreotide at least 30 minutes after administering Xermelo. (2, 7.1)
- Discontinue Xermelo if severe constipation develops. (2, 5.1)

3 DOSAGE FORMS AND STRENGTHS

Tablets: 250 mg telotristat ethyl (3)

4 CONTRAINDICATIONS

None. (4)

5 WARNINGS AND PRECAUTIONS

Constipation: Xermelo reduces bowel movement frequency; monitor patients for constipation and/or severe persistent or worsening abdominal pain. Discontinue Xermelo if severe constipation or abdominal pain develops. (5.1)

6 ADVERSE REACTIONS

Most common adverse reactions (≥5%) are nausea, headache, increased GGT, depression, flatulence, decreased appetite, peripheral edema, and pyrexia. (6.1)

To report SUSPECTED ADVERSE REACTIONS, contact TerSera Therapeutics LLC at 1-844-334-4035 or FDA at 1-800-FDA-1088 or www.fda.gov/medwatch

7 DRUG INTERACTIONS

CYP3A4 Substrates (e.g., midazolam): Efficacy of concomitant drugs may be decreased; monitor for suboptimal efficacy and consider increasing the dose of the concomitant drug. (7.1)

FULL PRESCRIBING INFORMATION

1 INDICATIONS AND USAGE

Xermelo is indicated for the treatment of carcinoid syndrome diarrhea in combination with somatostatin analog (SSA) therapy in adults inadequately controlled by SSA therapy.

2 DOSAGE AND ADMINISTRATION

The recommended dosage of Xermelo in adult patients is 250 mg three times daily for patients whose diarrhea is inadequately controlled by SSA therapy.

Administration

- Take Xermelo with food [see Clinical Pharmacology (12.3), Clinical Studies (14)].
- When short-acting octreotide is used in combination with Xermelo, administer short-acting octreotide at least 30 minutes after administering Xermelo [see Clinical Pharmacology (12.3), Clinical Studies (14)].
- If a dose is missed, take the next dose at the regular time. Do not take 2 doses at the same time to make up for a missed dose.
- Discontinue Xermelo if severe constipation develops [see Warnings and Precautions (5.1)].

3 DOSAGE FORMS AND STRENGTHS

Tablets: 250 mg telotristat ethyl; white to off-white, coated and oval with “T-E” debossed on one side and “250” debossed on the other side.

4 CONTRAINDICATIONS

None.

5 WARNINGS AND PRECAUTIONS

5.1 Constipation

Xermelo reduces bowel movement frequency. In a 12-week, placebo-controlled trial, in which patients had 4 or greater bowel movements per day, 2 out of 45 patients treated with a higher than recommended dosage of Xermelo reported constipation. In one patient the constipation was serious, resulting in hospitalization. During the 36-week extension period with higher than the recommended dosage, 10 of 115 patients reported constipation: one developed intestinal perforation and one developed obstruction. In another 12-week, placebo-controlled trial in which patients had less than 4 bowel movements per day, 4 out of 25 patients treated with the recommended dosage of Xermelo reported constipation. Given that patients with metastatic carcinoid tumors may have impaired integrity of the gastrointestinal tract wall, monitor for the development of constipation and/or severe, persistent, or worsening abdominal pain in patients taking Xermelo. Discontinue Xermelo if severe constipation or severe persistent or worsening abdominal pain develops [see Dosage and Administration (2), Adverse Reactions (6.1)].

6 ADVERSE REACTIONS

6.1 Clinical Trials Experience

Because clinical trials are conducted under widely varying conditions, adverse reaction rates observed in the clinical trials of a drug cannot be directly compared to rates in the clinical trials of another drug and may not reflect the rates observed in practice.

Xermelo was studied in a double-blind, placebo-controlled clinical trial of 90 patients with metastatic neuroendocrine tumors and carcinoid syndrome diarrhea. Patients reported between 4 to 12 bowel movements daily despite the use of SSA therapy at a stable dose for at least 3 months [see Clinical Studies (14)]. Placebo or Xermelo 250 mg was administered three times daily for 12 weeks. Concomitant anti-diarrheal medications (e.g., loperamide) were used by 43% (36% and 51% in the placebo and Xermelo group, respectively), pancreatic enzyme replacement medications by 39% (36% and 42% in the placebo and Xermelo group, respectively), and opioid analgesics by 29% (24% and 33% in the placebo and Xermelo group, respectively) of patients during the 12-week double-blind period of the trial.

Table 1 below lists adverse reactions occurring at an incidence of at least 5% in the Xermelo group (N=45) and at an incidence greater than placebo (N=45) during the 12-week placebo-controlled period of the trial.

Table 1: Percent Common Adverse Reactionsa by Treatment Group at 12-Weeks in a Double-Blind Placebo-Controlled Clinical Trial of Patients with Carcinoid Syndrome Diarrhea
Adverse Reaction | Xermelo 250 mg Three Times Daily, N=45 (%) | Placebo, N=45 (%)
Nausea | 13 | 11
Headache | 11 | 4
Increased gamma-glutamyl-transferase (GGT) | 9 | 0
Depressionb | 9 | 7
Peripheral edema | 7 | 2
Flatulence | 7 | 2
Decreased appetite | 7 | 4
Pyrexia | 7 | 4
a incidence of at least 5% in the Xermelo group and at an incidence greater than placebo
b including depression, depressed mood and decreased interest

In another placebo-controlled clinical trial of patients with carcinoid syndrome diarrhea and less than 4 bowel movements per day, the following additional adverse reactions, not listed in Table 1, of abdominal pain (including upper and lower abdominal pain, abdominal distention and gastrointestinal pain) and constipation were reported in at least 5% of patients in the Xermelo treated group and at an incidence greater than placebo [see Warnings and Precautions (5.1)].

Less Common Adverse Reactions:

The following is a list of adverse reactions occurring in less than 5% of patients receiving Xermelo during the 12-week placebo-controlled period of the clinical trial:

Investigations: increased alkaline phosphatase, increased alanine aminotransferase, and increased aspartate aminotransferase.

Fecaloma was reported in one patient treated with Xermelo during the 36-week open-label extension period following the 12-week double-blind period of the trial.

7 DRUG INTERACTIONS

7.1 CYP3A4 Substrates

Concomitant use of Xermelo may decrease the efficacy of drugs that are CYP3A4 substrates (e.g., midazolam) by decreasing their systemic exposure. Monitor for suboptimal efficacy and consider increasing the dose for concomitant CYP3A4 substrates, if necessary [see Clinical Pharmacology (12.3)].

7.2 Short-Acting Octreotide

Concurrent administration of short-acting octreotide with Xermelo significantly decreased the systemic exposure of telotristat ethyl and telotristat, the active metabolite. If treatment with short-acting octreotide is needed in combination with Xermelo, administer short-acting octreotide at least 30 minutes after administration of Xermelo [see Clinical Pharmacology (12.3), Clinical Studies (14)].

8 USE IN SPECIFIC POPULATIONS

8.1 Pregnancy

Risk Summary

There are no human data with Xermelo use in pregnant women to inform a drug-associated risk. In animal reproduction studies, no effects on embryo-fetal development were observed with the administration of oral telotristat ethyl to rats during organogenesis at doses up to 750 mg/kg/day (approximately 9 times the exposure at the RHD [recommended human dose]). Treatment of pregnant rabbits with oral telotristat ethyl during organogenesis produced maternal toxicity and post-implantation loss at doses of 250 mg/kg/day or higher (approximately 15 times the exposure at the RHD), and reduced fetal weight at 500 mg/kg/day (approximately 33 times the exposure at the RHD). In a pre-/postnatal development study, an increased incidence of mortality in rat offspring was observed during postnatal days 0 to 4 at the maternal oral dose of 500 mg/kg/day (approximately 5 times the exposure at the RHD), given during organogenesis through lactation [see Data].

The estimated background risk of major birth defects and miscarriage for the indicated population is unknown. All pregnancies have a background risk of birth defect, loss or other adverse outcomes. In the U.S. general population, the estimated background risk of major birth defects and miscarriage in clinically recognized pregnancies is 2% to 4% and 15% to 20%, respectively.

Data

Animal data

An embryo-fetal development study performed in rats with oral telotristat ethyl at doses up to 750 mg/kg/day (approximately 9 times the AUC [area under the plasma concentration-time curve] for the active metabolite at the RHD) during organogenesis produced no harm to embryo-fetal development.

In pregnant rabbits treated orally with telotristat ethyl during organogenesis, an increased incidence of post-implantation loss at doses of 250 and 500 mg/kg/day (approximately 15 times the AUC for the active metabolite at RHD) and a decrease in fetal weight at 500 mg/kg/day (approximately 33 times the AUC for the active metabolite at the RHD) was observed. The adverse effects on embryo-fetal development were associated with maternal toxicity (impaired weight gain and/or mortality) at 250 and 500 mg/kg/day. No adverse effects on embryo-fetal development were observed at 125 mg/kg/day (approximately 5 times the AUC for the active metabolite at the RHD).

A pre-/postnatal development study was conducted in rats using oral administration of 100, 200, and 500 mg/kg/day telotristat ethyl during organogenesis through lactation. An increased incidence of pup mortality was observed during postnatal days 0 to 4 at the maternal dose of 500 mg/kg/day (approximately 5 times the AUC for the active metabolite at the RHD). No developmental abnormalities or effects on growth, learning and memory, or reproductive performance were observed through maturation of offspring at maternal doses of up to 500 mg/kg/day in surviving offspring.

8.2 Lactation

Risk Summary

There are no data on the presence of telotristat ethyl in human or animal milk, the effects on the breastfed infant, or the effects on milk production. The effects of local gastrointestinal and systemic exposure to telotristat ethyl on breastfed infants are unknown. The developmental and health benefits of breastfeeding should be considered along with the mother's clinical need for Xermelo and any potential adverse effects on the breastfed infant from Xermelo or from the underlying maternal condition.

Clinical Considerations

Monitor the breastfed infant for symptoms of constipation.

8.4 Pediatric Use

The safety and effectiveness of Xermelo in pediatric patients have not been established.

8.5 Geriatric Use

Of 45 patients in a clinical trial of Xermelo, 19 (42%) patients were 65 years of age and over. No overall differences in safety or effectiveness were observed between these patients and younger patients, and other reported clinical experience has not identified differences in responses between the elderly and younger patients, but greater sensitivity of some older individuals cannot be ruled out.

11 DESCRIPTION

Xermelo (telotristat ethyl) tablets contain telotristat ethyl as telotristat etiprate, a tryptophan hydroxylase inhibitor. Telotristat etiprate is the hippurate salt of telotristat ethyl [(S)-ethyl 2-amino-3-(4-(2-amino-6-((R)-1-(4-chloro-2-(3-methyl-1H-pyrazol-1-yl)phenyl)-2,2,2-trifluoroethoxy)pyrimidin-4-yl)phenyl)propanoate], which undergoes hydrolysis to the active metabolite, (S)-2-amino-3-(4-(2-amino-6-((R)-1-(4-chloro-2-(3-methyl-1H-pyrazol-1-yl)phenyl)-2,2,2-trifluoroethoxy)pyrimidin-4-yl)phenyl)propanoic acid.

The molecular formula of telotristat etiprate is C27H26ClF3N6O3 • C9H9NO3 and its molecular weight is 754.2. The molecular weight of the free base (telotristat ethyl) is 575.0.

Chemical Structure:

Telotristat etiprate is a white to off-white solid. The solubility is a function of pH at 25°C; at pH 1 (0.1N HCl), the solubility is greater than 71 mg/mL, at pH 3 phosphate buffer, the solubility is 0.30 mg/mL, at a pH of 5 to 9, the solubility is negligible. In organic solvents, telotristat etiprate is freely soluble in methanol, soluble in acetone, and sparingly soluble in ethanol.

Each Xermelo tablet contains 250 mg of telotristat ethyl (free base) which is equivalent to 328 mg telotristat etiprate. The inactive ingredients of Xermelo tablets include: colloidal silicon dioxide, croscarmellose sodium, hydroxypropyl cellulose, lactose anhydrous, macrogol/PEG, magnesium stearate, polyvinyl alcohol [part hydrolyzed], talc and titanium dioxide.

12 CLINICAL PHARMACOLOGY

12.1 Mechanism of Action

Telotristat, the active metabolite of telotristat ethyl, is an inhibitor of tryptophan hydroxylase, which mediates the rate limiting step in serotonin biosynthesis. The in vitro inhibitory potency of telotristat towards tryptophan hydroxylase is 29 times higher than that of telotristat ethyl. Serotonin plays a role in mediating secretion, motility, inflammation, and sensation of the gastrointestinal tract, and is over-produced in patients with carcinoid syndrome. Through inhibition of tryptophan hydroxylase, telotristat and telotristat ethyl reduce the production of peripheral serotonin, and the frequency of carcinoid syndrome diarrhea.

12.2 Pharmacodynamics

In healthy subjects, telotristat ethyl 500 mg three times daily (twice the recommended dosage) for 14 days decreased whole blood serotonin and 24-hour urinary 5-hydroxyindolacetic acid (u5-HIAA) from baseline. A decrease in 24-hour u5-HIAA was observed as early as after 5 days of treatment.

In patients with metastatic neuroendocrine tumors and carcinoid syndrome diarrhea, 24-hour u5-HIAA decreased from baseline following 6 and 12 weeks of treatment with Xermelo 250 mg three times a day, whereas placebo did not decrease u5-HIAA.

Cardiac Electrophysiology

At a dose 6 times the recommended dose of 250 mg, Xermelo does not prolong the QT interval to any clinically relevant extent.

12.3 Pharmacokinetics

Absorption

After a single oral dose of telotristat ethyl to healthy subjects, telotristat ethyl was absorbed and metabolized to its active metabolite, telotristat. Peak plasma concentrations of telotristat ethyl were achieved within 0.5 to 2 hours, and those of telotristat within 1 to 3 hours. Plasma concentrations thereafter declined in a biphasic manner. Following administration of a single 500 mg dose of telotristat ethyl (twice the recommended dosage) under fasted conditions in healthy subjects, the mean Cmax and AUC0-inf were 4.4 ng/mL and 6.23 ng•hr/mL, respectively for telotristat ethyl. The mean Cmax and AUC0-inf were 610 ng/mL and 2320 ng•hr/mL, respectively for telotristat. Peak plasma concentrations and AUC of telotristat ethyl and telotristat appeared to be dose proportional following administration of a single dose of telotristat ethyl in the range of 100 mg (0.4 times the lowest recommended dose to 1000 mg [4 times the highest recommended dose]) under fasted conditions.

Following multiple-dose administration of telotristat ethyl 500 mg three times daily, there was negligible accumulation at steady state for both telotristat ethyl and telotristat.

In patients with metastatic neuroendocrine tumors and carcinoid syndrome diarrhea treated with SSA therapy, the median Tmax for telotristat ethyl and telotristat was approximately 1 and 2 hours, respectively. Following administration of 500 mg telotristat ethyl three times daily, with meals in patients, the mean Cmax and AUC0-6hr were approximately 7 ng/mL and 22 ng•hr/mL, respectively, for telotristat ethyl. The mean Cmax and AUC0-6hr were approximately 900 ng/mL and 3000 ng•hr/mL, respectively for telotristat. The pharmacokinetic parameters for both telotristat ethyl and telotristat were highly variable with about 55% coefficient of variation.

Food Effect

Administration of a single 500 mg dose of Xermelo (twice the recommended dose) with food resulted in higher exposure to both telotristat ethyl and telotristat. The systemic exposure to telotristat ethyl, was significantly increased following administration with a high-fat meal, with Cmax, and AUC0-inf being 112%, and 264% higher, respectively compared to the fasted state. Following administration of a single 500 mg dose of telotristat ethyl under the fed conditions in healthy subjects, the mean Cmax and AUC0-inf were 10.5 ng/mL and 21.6 ng•hr/mL, respectively for telotristat ethyl. The Cmax and AUC0-inf values for telotristat were also increased by 47% and 33%, respectively, with a high-fat meal compared to the fasted state. The mean Cmax and AUC0-inf were 908 ng/mL and 2980 ng•hr/mL, respectively for telotristat under the fed condition. [see Dosage and Administration (2)].

Distribution

Both telotristat ethyl and telotristat are greater than 99% bound to human plasma proteins.

In vitro data suggests that telotristat is a substrate of P-glycoprotein.

Elimination

Following a single 500 mg oral dose of telotristat ethyl in healthy subjects, the apparent half-life was approximately 0.6 hours for telotristat ethyl and 5 hours for telotristat. The apparent total clearance at steady state (CL/Fss) following oral dosing with telotristat ethyl 500 mg three times daily for 14 days (twice the recommended dosage) in healthy subjects was 2.7 and 152 L/hr for telotristat ethyl and telotristat, respectively.

Metabolism

After oral administration, telotristat ethyl undergoes hydrolysis via carboxylesterases to telotristat, its active metabolite. Telotristat is further metabolized. Among the metabolites of telotristat, the systemic exposure to an acid metabolite of oxidative deaminated decarboxylated telotristat was about 35% of that of telotristat. In vitro data suggest that telotristat ethyl and telotristat are not substrates for CYP enzymes.

Excretion

Following a single 500 mg oral dose of ^14C-telotristat ethyl, 93.2% of the dose was recovered over 240 hours: 92.8% was recovered in the feces, with less than 0.4% being recovered in the urine.

Specific Populations

Age and Sex

Population pharmacokinetic analysis indicated that age (18 to 83 years) and sex do not affect the pharmacokinetics of telotristat.

Renal Impairment

Population pharmacokinetic analysis indicated that creatinine clearance (20 to 89 mL/min) does not affect the pharmacokinetics of telotristat. Xermelo was not studied in end-stage renal disease (ESRD) patients who require dialysis.

Hepatic Impairment

Population pharmacokinetic analysis indicated that mild hepatic impairment (defined as total bilirubin greater than 1 to 1.5 times the upper limit of normal [ULN] or AST greater than the ULN) does not affect the pharmacokinetics of telotristat. The effect of moderate or severe hepatic impairment (defined as total bilirubin greater than 1.5 times the ULN and any value for AST) is unknown.

Drug Interaction Studies

Effect of Telotristat Ethyl on Other Drugs

In vitro studies

The potential for telotristat ethyl and telotristat to induce CYP enzymes (1A2 and 2B6) or inhibit CYP enzymes (2B6, 2C8, and 2C9) has not been adequately studied in vitro.

In vitro telotristat ethyl inhibited P-glycoprotein (P-gp) and breast cancer resistance protein (BCRP), but telotristat did not inhibit P-gp and BCRP at the clinically relevant concentrations. However, in vivo drug interaction potential via inhibition of BCRP is low based on in vitro studies and in vivo findings.

Based on in vitro studies, in vivo drug interaction potential via inhibition of organic cation transporter 1 (OCT1), OCT2, organic anion transporter 1 (OAT1), OAT3, organic anion transporting polypeptide 1B1 (OATP1B1), OATP1B3, or bile salt export pump (BSEP) transporters by telotristat ethyl and telotristat is low at the recommended dosage.

Midazolam (sensitive CYP3A4 substrate)

Following administration of multiple doses of telotristat ethyl, the systemic exposure to concomitant midazolam was significantly decreased. When 3 mg midazolam was co-administered orally after 5 day treatment with telotristat ethyl 500 mg three times daily (twice the recommended dosage), the mean Cmax, and AUC0-inf for midazolam were decreased by 25%, and 48%, respectively, compared to administration of midazolam alone. The mean Cmax, and AUC0-inf for the active metabolite, 1'-hydroxymidazolam, were also decreased by 34%, and 48%, respectively. The reduction in the systemic exposure to both midazolam and its active metabolite suggests that the glucuronidation of 1'-hydroxymidazolam may have been increased by telotristat ethyl [see Drug Interactions (7.1)].

Fexofenadine (sensitive P-gp substrate)

The Cmax and AUC of fexofenadine increased by 16% when a single 180 mg dose of fexofenadine was co-administered orally with the final dose of telotristat ethyl 500 mg administered three times daily (twice the recommended dosage) for 5 days. Clinically meaningful interactions with P-gp substrates are unlikely.

Effect of Other Drugs on Telotristat Ethyl

Short-Acting Octreotide

The mean Cmax and AUC0-last of telotristat ethyl were decreased by 86% and 81%, respectively, following administration of a single 500 mg dose of Xermelo (twice the recommended dose), co-administered with short-acting octreotide 200 mcg injected subcutaneously in healthy subjects. The mean Cmax and AUC0-last of telotristat were decreased by 79% and 68%, respectively [see Clinical Studies (14)].

13 NONCLINICAL TOXICOLOGY

13.1 Carcinogenesis, Mutagenesis, Impairment of Fertility

In a 26-week study in transgenic (Tg.rasH2) mice, telotristat ethyl was not tumorigenic at oral doses up to 300 mg/kg/day.

Telotristat ethyl was negative in the in vitro Ames test, the in vitro chromosomal aberration test using Chinese hamster ovary cells, and the in vivo rat micronucleus test.

Telotristat ethyl at oral doses up to 500 mg/kg/day (approximately 5 times the AUC for the active metabolite at the RHD) was found to have no effect on fertility and reproductive performance of male or female rats.

14 CLINICAL STUDIES

A 12-week double-blind, placebo-controlled, randomized, multicenter trial of Xermelo was conducted in adult patients with a well-differentiated metastatic neuroendocrine tumor and carcinoid syndrome diarrhea who were having between 4 to 12 daily bowel movements despite the use of SSA therapy at a stable dose for at least 3 months. Patients were randomized to placebo or treatment with Xermelo 250 mg three times daily.

Study medication was administered within 15 minutes before or within 1 hour after a meal or snack [see Dosage and Administration (2)]. All patients were required to stay on their baseline SSA regimen and were allowed to use rescue medication (short-acting octreotide) and antidiarrheals (e.g., loperamide) for symptomatic relief. A total of 90 patients were evaluated for efficacy. The mean age of the population was 63 years of age (range 37 to 83 years), 50% were male, and 90% were White.

The primary efficacy endpoint was the change from baseline in the number of daily bowel movements averaged over the 12-week treatment period. The analysis results can be found in Table 2 below. The average was based on the number of days with valid, non-missing data. When a patient had more than 6 weeks of missing data, the change from baseline was considered equal to zero. A week of missing data was defined as a patient missing at least 4 days of diary data in that week.

Table 2: Change from Baseline in Bowel Movements/Day Averaged Over 12 Weeks in Adult Patients with Carcinoid Syndrome Diarrhea
 | Parameter | Xermelo 250 mg three times daily | Placebo
Bowel Movements/Day At Baselinea | Number of Patients | 45 | 45
Bowel Movements/Day At Baselinea | Baseline Mean (SD) Median (Min, Max) | 6.1 (2.1) 5.5 (3.5, 13.0) | 5.2 (1.4) 5.1 (3.5, 9.0)
Change From Baseline In Bowel Movements/Day Averaged Over 12 Weeks | Change Averaged over 12 Weeks: Mean (SD) Median (Min, Max) | ˗1.4 (1.4) -1.3 (-6.1, 1.6) | ˗0.6 (0.8) -0.6 (-2.7, 0.8)
Change From Baseline In Bowel Movements/Day Averaged Over 12 Weeks | Estimate of Treatment Difference (97.5% CL)b | ˗0.8c (˗1.3, ˗0.3) | ---
CL=confidence limit; SD=standard deviation.
a Baseline Bowel Movements/Day was assessed over the 3-4 week screening/run-in period.
b Statistical tests used a blocked 2-sample Wilcoxon Rank Sum statistic (van Elteren test) stratified by the u5-HIAA stratification at randomization. CLs were based on the Hodges-Lehmann estimator of the median paired difference.
c p<0.001

In the 12-week study, a difference in average weekly reductions in bowel movement frequency between Xermelo and placebo was observed as early as 1 to 3 weeks, and persisted for the remaining 9 weeks of the study.

To aid in the interpretation of the bowel movement reduction results, the proportion of patients reporting any particular level of reduction in overall average bowel movement frequency is depicted in Figure 1 below. For example, 33% of patients randomized to Xermelo and 4% of patients randomized to placebo experienced a reduction in overall average bowel movements from baseline of at least 2 bowel movements per day.

Figure 1: Cumulative Proportion of Patients with Carcinoid Syndrome Diarrhea Reporting Change in Overall Average Bowel Movement Frequency

Other symptoms of carcinoid syndrome (abdominal pain or flushing) did not show improvement in the comparison of Xermelo to placebo.

The average number of daily short-acting octreotide injections used for rescue therapy over the 12-week double-blind treatment period was 0.3 and 0.7 in the Xermelo and placebo groups, respectively. In the subgroup of patients who received short-acting octreotide injections, observed reductions in the number of bowel movements per day and treatment differences were generally consistent with the reductions and differences observed in patients who did not receive rescue therapy, and were similar to the overall data presented in Table 2 above [see Dosage and Administration (2), Drug Interactions (7.2)].

A third randomized treatment arm of Xermelo 500 mg three times daily did not demonstrate additional treatment benefit on the primary endpoint and had a greater incidence of adverse reactions than Xermelo 250 mg three times daily. Therefore, Xermelo 500 mg three times daily is not recommended [see Dosage and Administration (2)].

16 HOW SUPPLIED/STORAGE AND HANDLING

How Supplied

250 mg tablet: white to off-white coated oval tablet with “T-E” debossed on one side and “250” debossed on the other side.

Xermelo is dispensed in a monthly case for a total of 28 days of therapy. Each monthly case contains four weekly packs. Each weekly pack contains 21 tablets.

- NDC 70183-125-85: Monthly case of 84 tablets. Each child resistant weekly pack contains twenty one 250 mg tablets.

Storage

Store at 25°C (77°F); excursions permitted to 15°C to 30°C (59°F to 86°F) [see USP Controlled Room Temperature].

17 PATIENT COUNSELING INFORMATION

Advise patients:

- If they experience severe constipation or severe persistent or worsening abdominal pain, to discontinue Xermelo and contact their healthcare provider [see Warnings and Precautions (5.1)].
- To take Xermelo with food [see Clinical Pharmacology (12.3), Clinical Studies (14)].
- When short-acting octreotide is used in combination with Xermelo, administer short-acting octreotide at least 30 minutes after administering Xermelo [see Clinical Pharmacology (12.3), Clinical Studies (14)].
- If a dose is missed, take the next dose at the regular time. Do not take 2 doses at the same time to make up for a missed dose.

Distributed by:
Lexicon Pharmaceuticals, Inc.
The Woodlands, TX 77381

PACKAGE LABEL

Principal Display Panel - 3x7 weekly pack

TO OPEN:

1 Press & hold button

2 Pull out card

WEEKLY PACK
21 TABLETS
Rx Only

XERMELO®
(telotristat ethyl) tablets

250 mg
per tablet

Lexicon®
pharmaceuticals

For oral use only.
As with all medications, keep
out of reach of children.

NDC 70183-125-22

Principal Display Panel - 28 Day Case Label

NDC 70183-125-85
Rx Only

28 DAY CASE
84 TABLETS

XERMELO®
(telotristat ethyl) tablets

250 mg
per tablet

Lexicon®
pharmaceuticals

For oral use only.
As with all medications, keep out of reach of children.